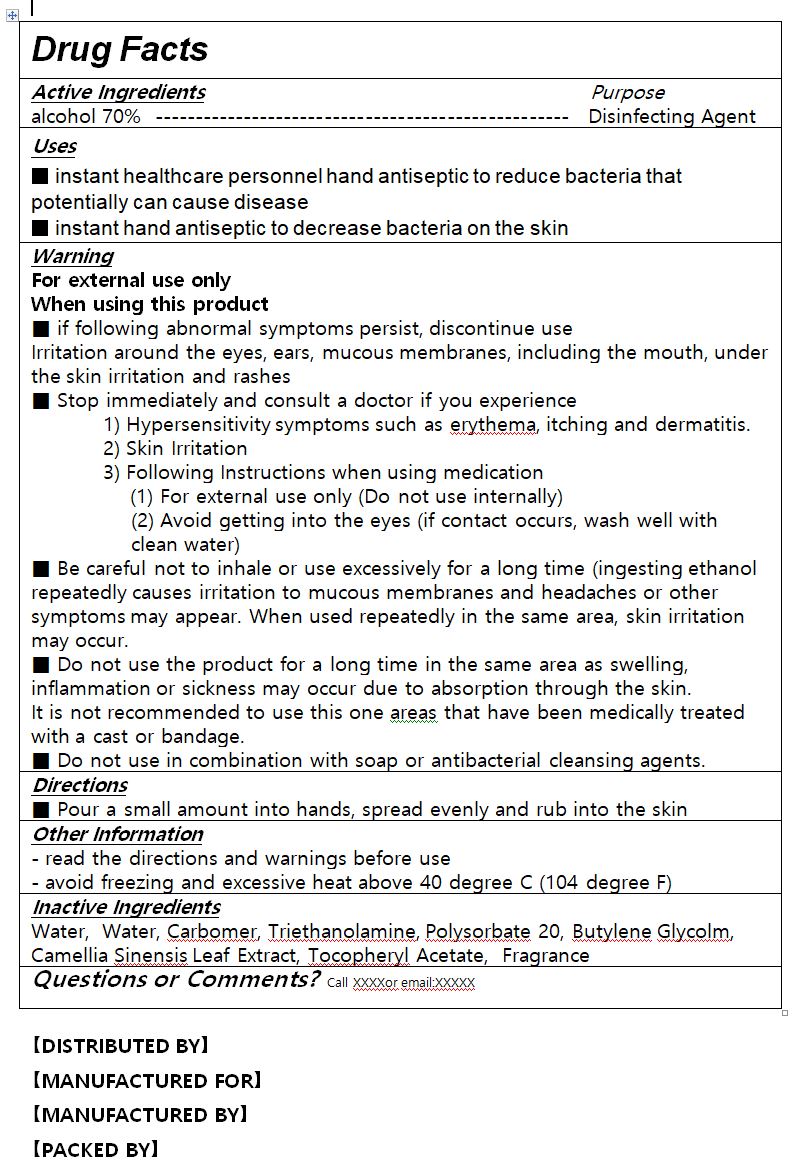 DRUG LABEL: Innovative Display Hand Sanitizer
NDC: 76586-114 | Form: GEL
Manufacturer: HEALKINBIO CO.
Category: otc | Type: HUMAN OTC DRUG LABEL
Date: 20200814

ACTIVE INGREDIENTS: ALCOHOL 70 mL/100 mL
INACTIVE INGREDIENTS: CARBOMER 940; TROLAMINE; .ALPHA.-TOCOPHEROL ACETATE; WATER; GREEN TEA LEAF; POLYSORBATE 20; BUTYLENE GLYCOL

Active Ingredient(s)

alcohol

Purpose

Purpose: Antiseptic

Use

 Hand sanitizing to help reduce bacteria on the skin

Warnings

 For external use only.
 Flammable, keep away from fire or flame.
 When using this product, avoid contact with the eyes. In case of contact, rinse eyes thoroughly with water.
 Stop use and ask a doctor if irritation or redness appears and lasts.

 Keep out of reach of children. If swallowed, get medical help or contact a Poison Control Center immediately.

Directions

 Take suitable amount of sanitizer in the hand. Wet thoroughly and rub hands together until dry

Other information

 Store in room temperature 0~30℃

 Period of Use: 36 Months after manufacturing date

 Manufacturing Date and No. Printed on bottle

INACTIVE INGREDIENT

Water, Carbomer, Triethanolamine, Polysorbate 20, Butylene Glycolm, Camellia Sinensis Leaf Extract, Tocopheryl Acetate, Fragrance